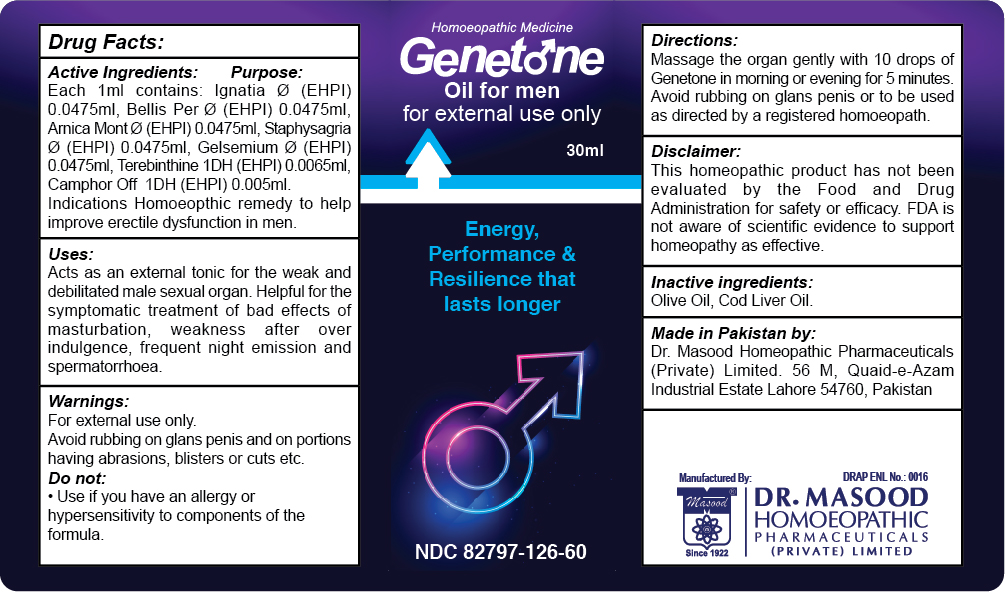 DRUG LABEL: Genetone Oil
NDC: 82797-126 | Form: OIL
Manufacturer: Dr. Masood Homeopathic Pharmaceuticals Private Limited
Category: homeopathic | Type: HUMAN OTC DRUG LABEL
Date: 20240423

ACTIVE INGREDIENTS: TEREBINTHONE 0.195 mg/30 mL; ARNICA MONTANA 1.425 mg/30 mL; DELPHINIUM STAPHISAGRIA WHOLE 1.425 mg/30 mL; CAMPHOR LEAF OIL 0.15 mg/30 mL; GELSEMINE 1.425 mg/30 mL; STRYCHNOS IGNATII SEED 1.425 mg/30 mL; BELLIS PERENNIS 1.425 mg/30 mL
INACTIVE INGREDIENTS: COD LIVER OIL 0.48 mg/30 mL; OLIVE OIL 0.525 mg/30 mL

Dosage and Administration

Massage the organ gently with 10 drops of Genetone oil for five minutes early morning or before going to bed.

Avoid rubbing on glans penis

Inactive Ingredients:

Olive Oil

Cod Liver Oil

indications and Usage

Homeopathic remedy to help improve erectile dysfunction in men

Acts as an external tonic for weak and debilitated male sexual organ

Helpful for the symptomatic treatment of bad effects of excessive masturbation

weakness after overindulgence in sexual activity, frequent night emissions and spermatorrhea

Active Ingredients:

Each 1 mi contains:

Ignatia Ø 0.0475 ml

Bellis Per Ø 0.0475 ml

Arnica Mont Ø 0.0475 ml

Staphysagria Ø 0.0475 ml

Gelsemium Ø 0.0475 ml

Terebinthina 1DH 0.0065 ml

Camphor Off 1DH 0.005 ML

KEEP OUT OF THE REACH OF CHILDREN

Keep this and all medicines out of the reach of children

Purpose:

Active Ingredient Purpose

Ignatia Ignatia seeds or whole plants are used as a nerve tonic, aphrodisiac, and stimulant

Bellis Per Helps in erectile dysfunction

Arnica Mont Impotence from excess or abuse

Staphysagria weakness and sexual neurasthenia.

Gelsemium Helps overcome involuntary emission of semen without an erection;

Terebinthina Improves blood circulation to the penis

Camphor Off 1DH Camphor interacts with the pleasure center of the body, and it affects the area of the brain which i is responsible for sexual stimulation. The oil of camphor can help with erectile dysfunction issues, by improving blood flow to the penis and stimulating the brain.

Warnings:

For external use only

Avoid rubbing on glans penis and on portions having abraisons, blisters or cuts

Do not:

use if you have an allergy or hypersensitivity to any of the ingredients in this formulation